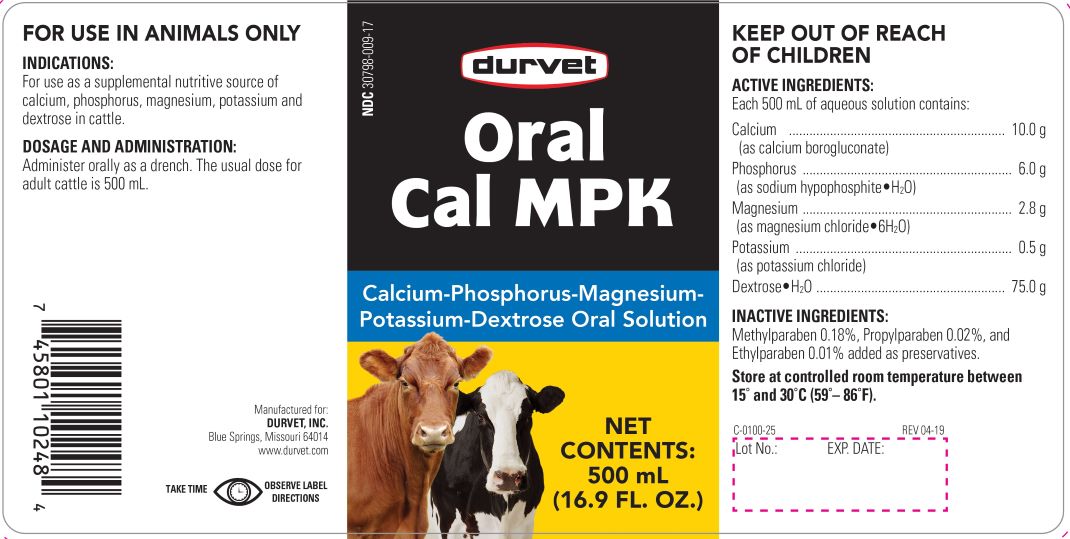 DRUG LABEL: Oral Cal MPK
NDC: 30798-009 | Form: SOLUTION
Manufacturer: Durvet, Inc.
Category: animal | Type: OTC ANIMAL DRUG LABEL
Date: 20200211

ACTIVE INGREDIENTS: CALCIUM CARBONATE 9 g/500 mL; SODIUM HYPOPHOSPHITE MONOHYDRATE 5.4 g/500 mL; MAGNESIUM CHLORIDE 2.5 g/500 mL; POTASSIUM CHLORIDE 0.45 g/500 mL; DEXTROSE MONOHYDRATE 75 g/500 mL

CMPK Solution

INDICATIONS AND USAGE

Calcium-Phosphorus-Magnesium-Potassium-Dextrose Oral Solution

FOR ANIMAL USE ONLY

KEEP OUT OF REACH OF CHILDREN

INDICATIONS

For use as a supplemental nutritive source of calcium, phosphorus, magnesium, potassium and dextrose in cattle.

DOSAGE AND ADMINISTRATION

Administer orally as a drench. The usual dose for adult cattle is 500 mL.

STORAGE AND HANDLING

Store at controlled room temperature between 15° and 30°C (59°-86°F)

TAKE TIME OBSERVE LABEL DIRECTIONS

COMPONENTS

Active Ingredients:

Each 500 mL of aqueous solution contains:

Calcium ............................... 10.0 g

(as calcium borogluconate)

Phosphorus .......................... 6.0 g

(as sodium hypophosphite·H2O)

Magnesium ........................... 2.8 g

(as magnesium chloride·6H2O)

Potassium ............................ 0.5 g

(as potassium chloride)

Dextrose·H2O ..................... 75.0 g

Inactive Ingredients: methylparaben 0.18%, propylparaben 0.02%, and ethylparaben 0.01% added as preservatives.